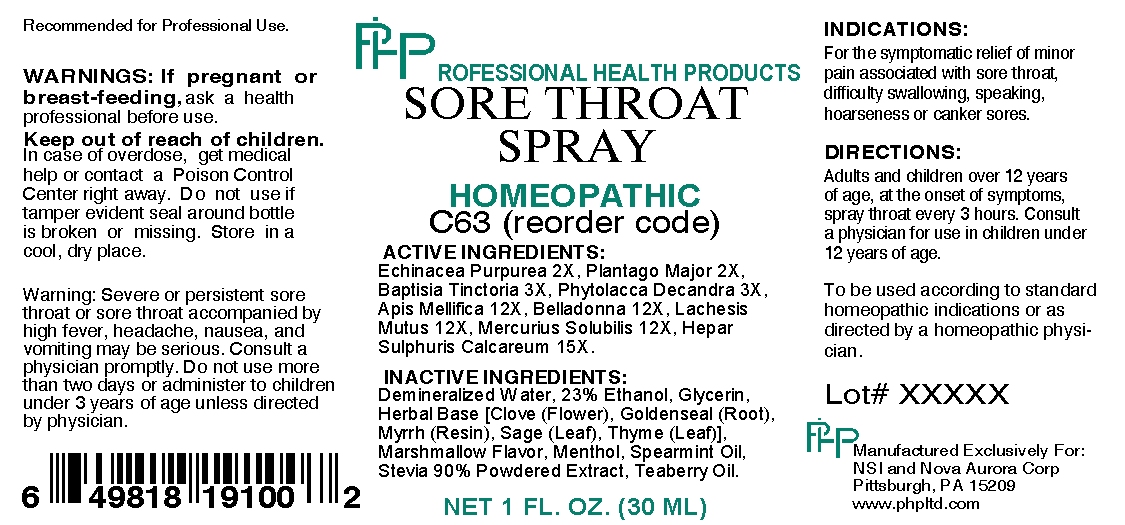 DRUG LABEL: Sore Throat 
NDC: 57520-0157 | Form: SPRAY
Manufacturer: Apotheca Company
Category: homeopathic | Type: HUMAN OTC DRUG LABEL
Date: 20100629

ACTIVE INGREDIENTS: ECHINACEA PURPUREA 2 [hp_X]/1 mL; PLANTAGO MAJOR 2 [hp_X]/1 mL; BAPTISIA TINCTORIA ROOT 3 [hp_X]/1 mL; PHYTOLACCA AMERICANA ROOT 3 [hp_X]/1 mL; APIS MELLIFERA 12 [hp_X]/1 mL; ATROPA BELLADONNA 12 [hp_X]/1 mL; LACHESIS MUTA VENOM 12 [hp_X]/1 mL; MERCURIUS SOLUBILIS 12 [hp_X]/1 mL; CALCIUM SULFIDE 15 [hp_X]/1 mL
INACTIVE INGREDIENTS: CLOVE; GOLDENSEAL; MYRRH; SAGE; THYME; WATER; ALCOHOL; GLYCERIN; MENTHOL; SPEARMINT OIL; STEVIA LEAF; METHYL SALICYLATE

Sore Throat Spray

ACTIVE INGREDIENT

ACTIVE INGREDIENTS: Echinacea purpurea 2X, Plantago major 2X, Baptisia tinctoria 3X, Phytolacca decandra 3X, Apil mellifica 12X, Belladonna 12X, Lachesis mutus 12X, Mercurius solubilis 12X, Hepar sulphuris calcareum 15X.

PURPOSE

INDICATIONS: For the symptomatic relief of monor pain associated with sore throat, difficulty swallowing, speaking, hoarseness or canker sores.

WARNINGS

WARNINGS: If pregnant or breast-feeding, ask a health professional before use.

Keep out of reach of children. In case of overdose, get medical help or contact a Poison Control Center right away. Do not use if tamper evident seal is broken or missing. Store in a cool, dry place.

WARNING: Severe or persistent sore throat or sore throat accompanied by high fever, headache, nausea, and vomiting may be serious. Consult a physician promptly. Do not use more that two days or administer to children under 3 years of age unless directed by a physician.

Recommended for Professional Use.

DOSAGE AND ADMINISTRATION

DIRECTIONS: Adults and children over 12 years of age, at onset of symptoms, spray throat every 3 hours. Consult a physician for use in children under 12 years of age.

To be used according to standard homeopathic indications or as directed by a homeopathic physician.

INACTIVE INGREDIENT

INACTIVE INGREDIENTS: Demineralized water, 23% Ethanol, Glycerin, Herbal Base [Clove (Flower), Goldenseal (Root), Myrrh (Resin), Sage (Leaf), Thyme (Leaf)], Marshmallow flavor, Menthol, Spearmint oil, Stevia 90% Powered Extract, Teaberry oil.

QUESTIONS

Manufactured Exclusively For:

NSI and Nova Aurora Corp

Pittsburgh, PA 15209

www.phpltd.com

PACKAGE LABEL

PROFESSIONAL HEALTH PRODUCTS

SORE THROAT SPRAY

HOMEOPATHIC

C63 (reorder code)

NET 1 FL. OZ. (30 ML)